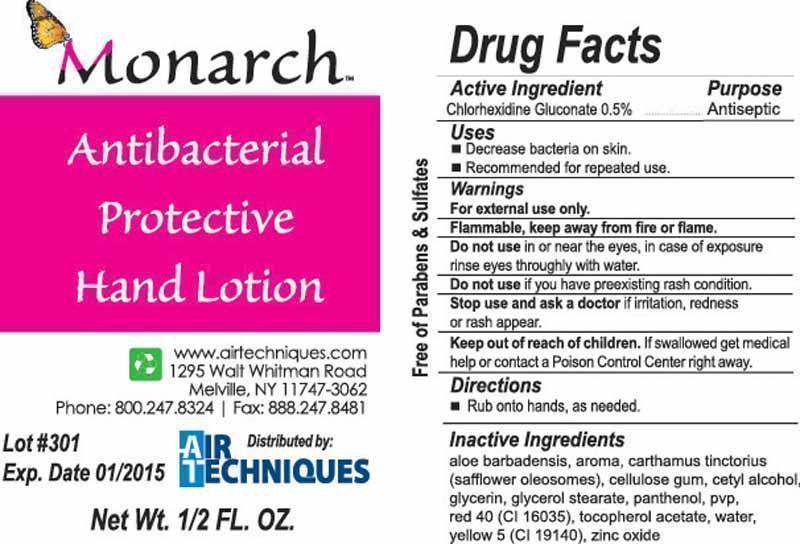 DRUG LABEL: Antibacterial Protective Hand
NDC: 51811-066 | Form: LOTION
Manufacturer: Hanover Pen Corp dba HPC Global
Category: otc | Type: HUMAN OTC DRUG LABEL
Date: 20130201

ACTIVE INGREDIENTS: CHLORHEXIDINE GLUCONATE .07075 g/14.15 g
INACTIVE INGREDIENTS: ALOE VERA FLOWER; CARTHAMUS TINCTORIUS (SAFFLOWER) OLEOSOMES; CARBOXYMETHYLCELLULOSE SODIUM; CETYL ALCOHOL; GLYCERIN; GLYCERYL MONOSTEARATE; PANTHENOL; POVIDONE K30; FD&C RED NO. 40; .ALPHA.-TOCOPHEROL ACETATE   ; WATER; FD&C YELLOW NO. 5; ZINC OXIDE

Drug Facts

Active Ingredient

Chlorhexidine Gluconate 0.5%

Purpose

Antiseptic

Uses

Decrease bacteria on skin.

Recommended for repeated use.

Warnings

For external use only.

Flammable, keep away from fire or flame.

Do not use in or near the eyes, in case of exposure rinse eyes throughly with water.

Do not use if you have preexisting rash condition.

Stop use and ask a doctor if irritation, redness or rash appear.

Keep out of reach of children. If swallowed get medical help or contact Poison Control Center right away.

Directions

Rub onto hands, as needed.

Inactive Ingredients

aloe barbadensis, aroma, carthamus tinctorius (safflower oleosomes), cellulose gum, cetyl alcohol, glycerin, glycerol stearate, panthenol, pvp, red 40 (ci 16035), tocopherol acetate, water, yellow 5 (CI 19140), zinc oxide

Drug Facts